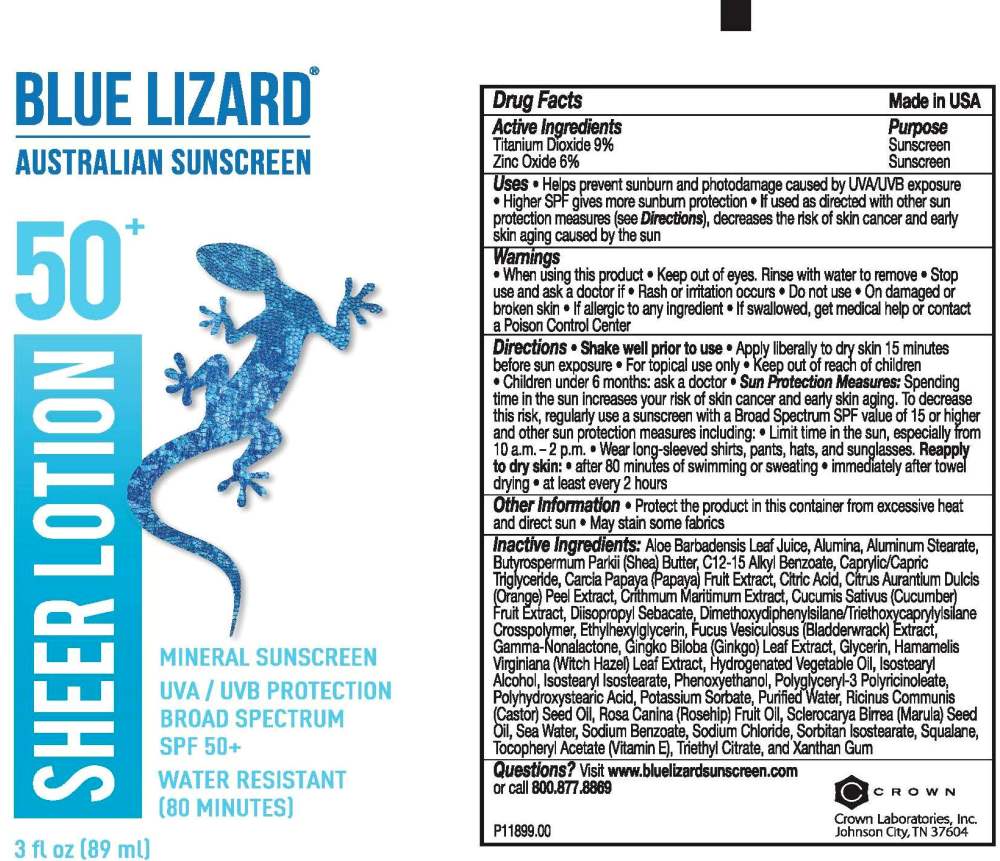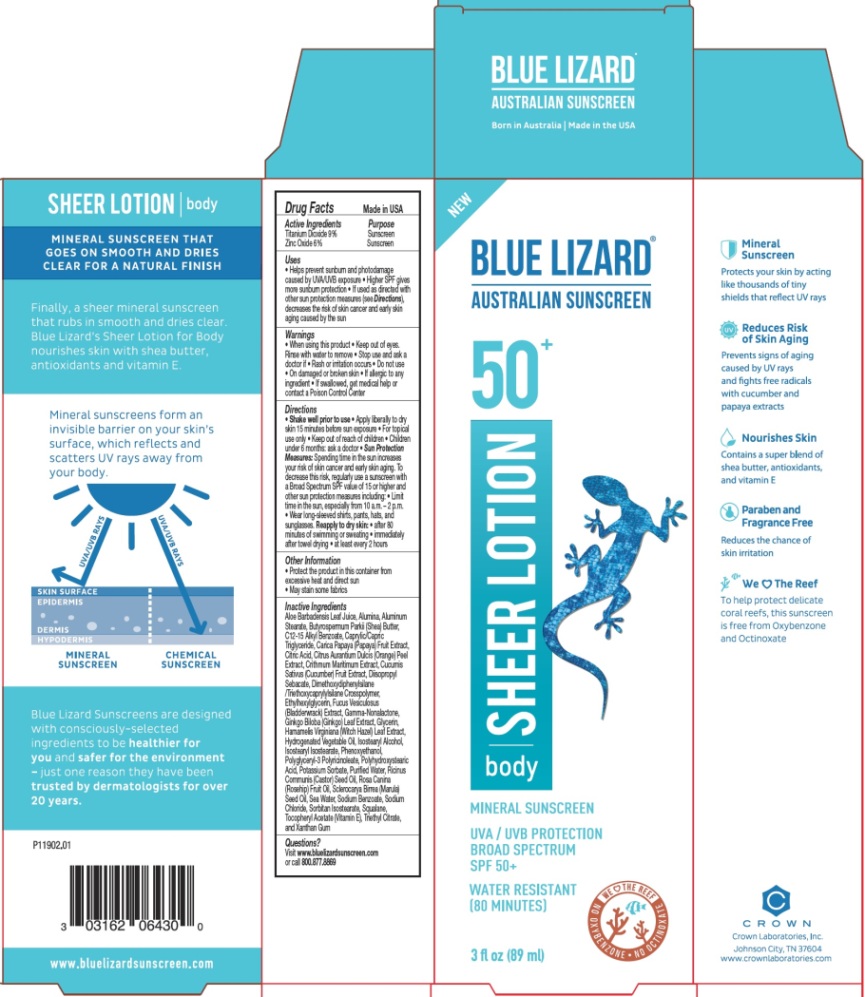 DRUG LABEL: Blue Lizard Sheer SPF 50 Sunscreen
NDC: 0316-2064 | Form: LOTION
Manufacturer: Crown Laboratories
Category: otc | Type: HUMAN OTC DRUG LABEL
Date: 20260112

ACTIVE INGREDIENTS: ZINC OXIDE 66.6 mg/1 mL; TITANIUM DIOXIDE 99.9 mg/1 mL
INACTIVE INGREDIENTS: HAMAMELIS VIRGINIANA LEAF; GINKGO; GLYCERIN; ALOE VERA LEAF; ALUMINUM OXIDE; ALUMINUM STEARATE; SHEA BUTTER; ALKYL (C12-15) BENZOATE; MEDIUM-CHAIN TRIGLYCERIDES; PAPAYA; CITRIC ACID MONOHYDRATE; ORANGE PEEL; CRITHMUM MARITIMUM WHOLE; CUCUMBER; DIISOPROPYL SEBACATE; DIMETHOXYDIPHENYLSILANE; TRIETHOXYCAPRYLYLSILANE; ETHYLHEXYLGLYCERIN; FUCUS VESICULOSUS; .GAMMA.-NONALACTONE; HYDROGENATED PALM OIL; HYDROGENATED RAPESEED OIL; ISOSTEARYL ISOSTEARATE; POTASSIUM SORBATE; WATER; CASTOR OIL; SCLEROCARYA BIRREA SEED OIL; SODIUM CHLORIDE; SORBITAN ISOSTEARATE; TRIETHYL CITRATE; XANTHAN GUM; SQUALANE; POLYGLYCERYL-3 PENTARICINOLEATE; .ALPHA.-TOCOPHEROL ACETATE; ISOSTEARYL ALCOHOL; PHENOXYETHANOL; POLYHYDROXYSTEARIC ACID (2300 MW); ROSA CANINA FRUIT OIL; SODIUM BENZOATE

Blue Lizard Sheer Lotion SPF 50 Sunscreen

Active Ingredients

Titanium Dioxide 9%

Zinc Oxide 6%

Purpose

Sunscreen

Uses

- Helps prevent sunburn and photodamage caused by UVA/UVB exposure
- Higher SPF gives more sunburn protection
- If used as directed with other sun protection measures (see Directions), decreases the risk of skin cancer and early skin aging caused by the sun

Warnings

- When using this product
- Keep out of eyes. Rinse with water to remove
- Stop use and ask a doctor if
- Rash or irritation occurs
- Do not use
- On damaged or broken skin
- If allergic to any ingredient
- If swallowed, get medical help or contact a Poison Control Center

Directions

- Shake well prior to use
- Apply liberally to dry skin 15 minutes before sun exposure
- For topical use only
- Keep out of reach of children
- Children under 6 months: ask a doctor
- Sun Protection Measures: Spending time in the sun increases your risk of skin cancer and early skin aging. To decrease this risk, regularly use a sunscreen with a Broad Spectrum SPF value of 15 or higher and other sun protection measures including:
- Limit time in the sun, especially from 10 a.m. - 2 p.m.
- Wear long-sleeved shirts, pants, hats, and sunglasses.
- Reapply to dry skin:
- after 80 minutes of swimming or sweating
- immediately after towel drying
- at least every 2 hours

Other Information

- Protect the product in this container from excessive heat and direct sun
- May stain some fabrics

Inactive Ingredients

Aloe Barbadensis Leaf Juice, Alumina, Aluminum Stearate, Butyrospermum Parkii (Shea) Butter, C12-15 Alkyl Benzoate, Caprylic/Capric Triglyceride, Carica Papaya (Papaya) Fruit Extract, Citric Acid, Citrus Aurantium Dulcis (Orange) Peel Extract, Crithmum Maritimum Extract, Cucumis Sativus (Cucumber) Fruit Extract, Diisopropyl Sebacate, Dimethoxydiphenylsilane/Triethoxycaprylylsilane Crosspolymer, Ethylhexylglycerin, Fucus Vesiculosus (Bladderwrack) Extract, Gamma-Nonalactone, Ginkgo Biloba (Ginkgo) Leaf Extract, Glycerin, Hamamelis Virginiana (Witch Hazel) Leaf Extract, Hydrogenated Vegetable Oil, Isostearyl Alcohol, Isostearyl Isostearate, Phenoxyethanol, Polyglyceryl-3 Polyricinoleate, Polyhydroxystearic Acid, Potassium Sorbate, Purified Water, Ricinus Communis (Castor) Seed Oil, Rosa Canina (Rosehip) Fruit Oil, Sclerocarya Birrea (Marula) Seed Oil, Sea Water, Sodium Benzoate, Sodium Chloride, Sorbitan Isostearate, Squalane, Tocopheryl Acetate (Vitamin E), Triethyl Citrate, and Xanthan Gum

Questions?

Visit www.bluelizardsunscreen.com or call 800.877.8869

Crown Laboratories, Inc., Johnson City, TN 37604

Blue Lizard Sheer Lotion - 3oz Tube Label

BLUE LIZARD

AUSTRALIAN SUNSCREEN

50+

Sheer Lotion

mineral sunscreen

UVA/UVB PROTECTION

BROAD SPECTRUM

SPF 50+

WATER RESISTANT (80 MINUTES)

P11899.00

Blue Lizard Sheer Lotion - 3oz Carton

BLUE LIZARD

AUSTRALIAN SUNSCREEN

50+

Sheer Lotion

body

mineral sunscreen

UVA/UVB PROTECTION

BROAD SPECTRUM

SPF 50+

WATER RESISTANT (80 MINUTES)

P11902.01